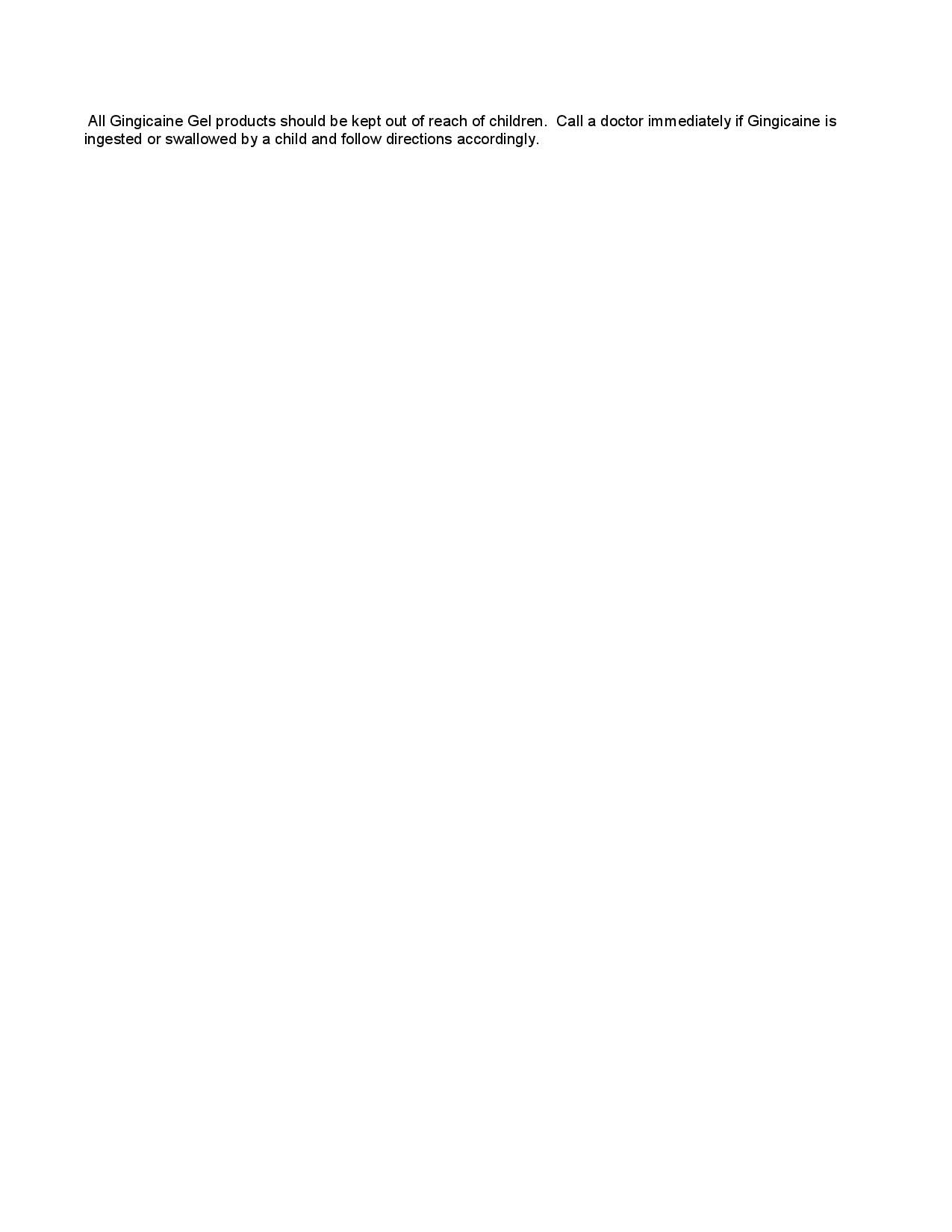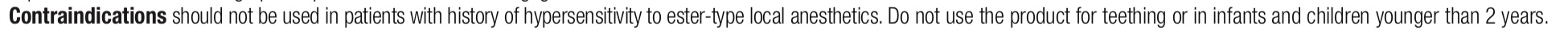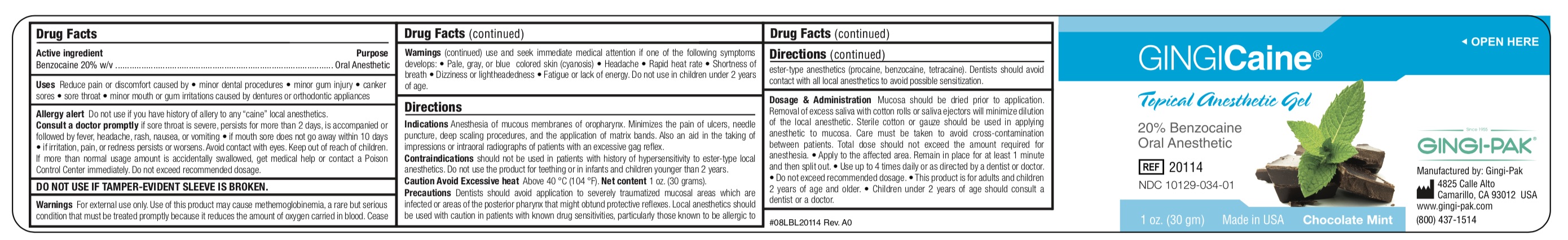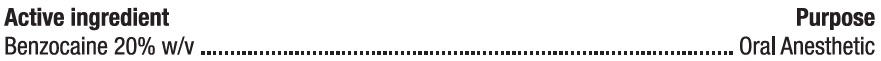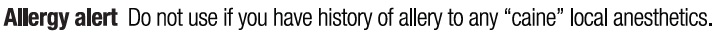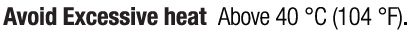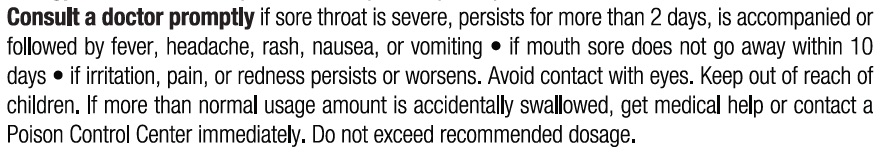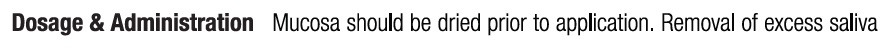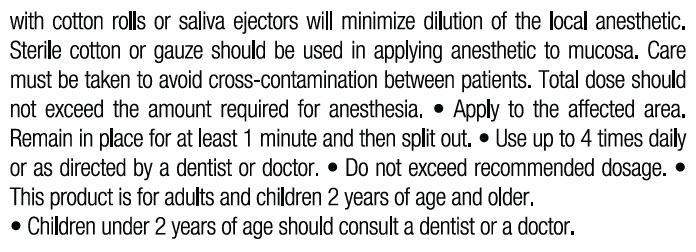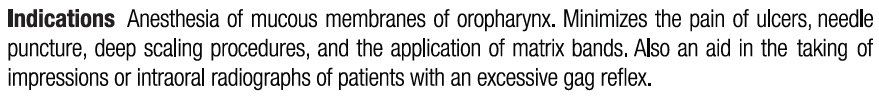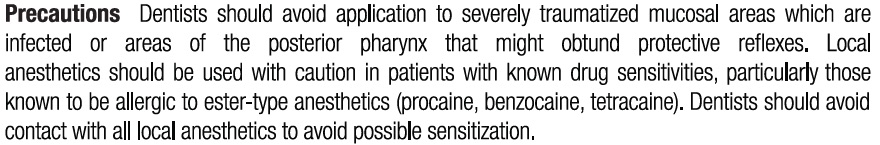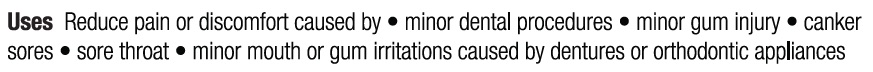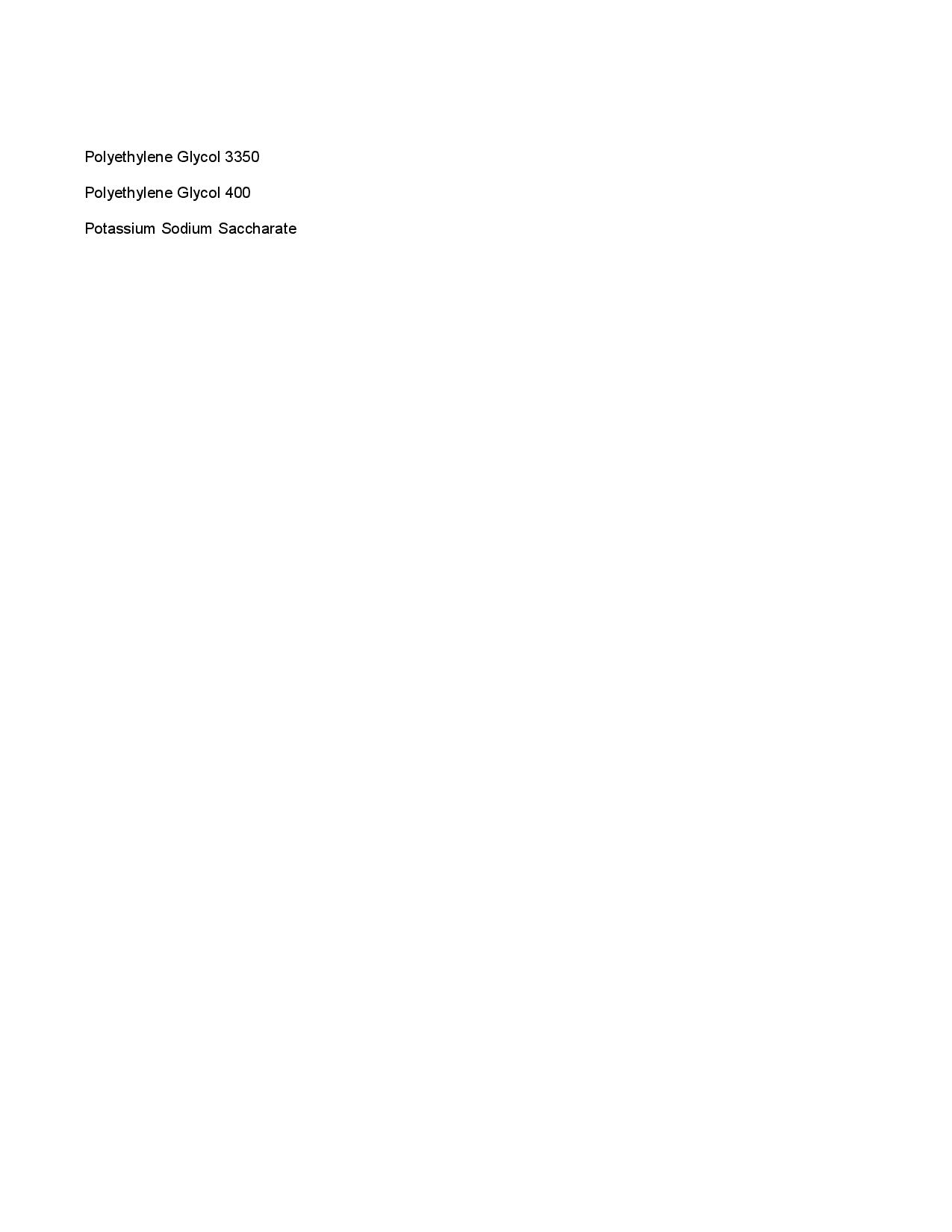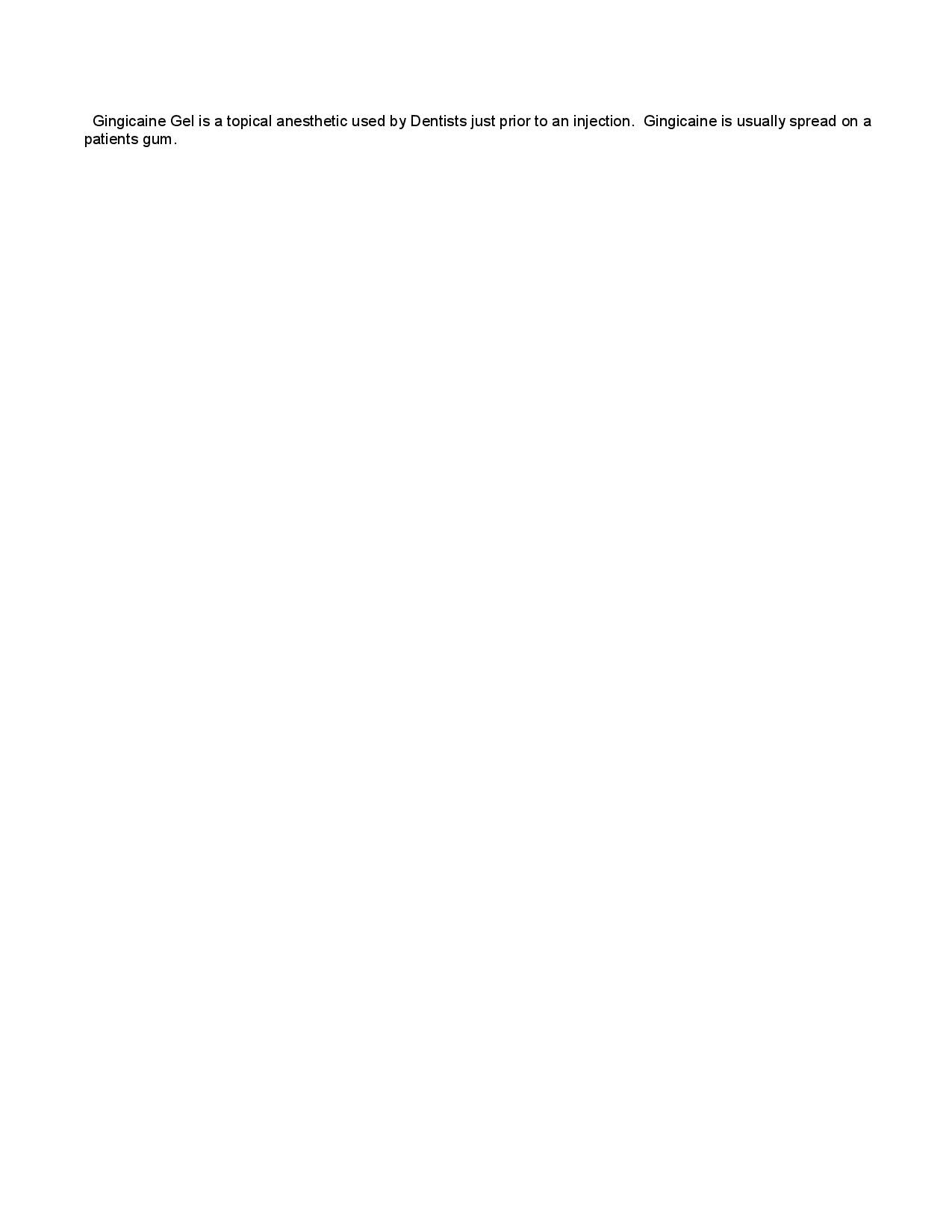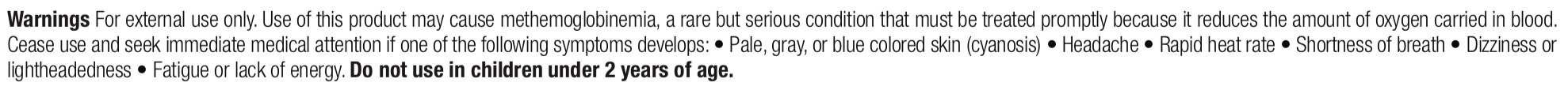 DRUG LABEL: GingiCaine Gel, Chocolate Mint
NDC: 10129-034 | Form: GEL
Manufacturer: Gingi-Pak a Division of the Belport
Category: otc | Type: HUMAN OTC DRUG LABEL
Date: 20211209

ACTIVE INGREDIENTS: BENZOCAINE 200 mg/1 1
INACTIVE INGREDIENTS: POLYETHYLENE GLYCOL 3350 260 mg/1 1; POLYETHYLENE GLYCOL 400 520 mg/1 1; POTASSIUM SODIUM SACCHARATE 20 mg/1 1

GingiCaine Gel, Chocolate Mint